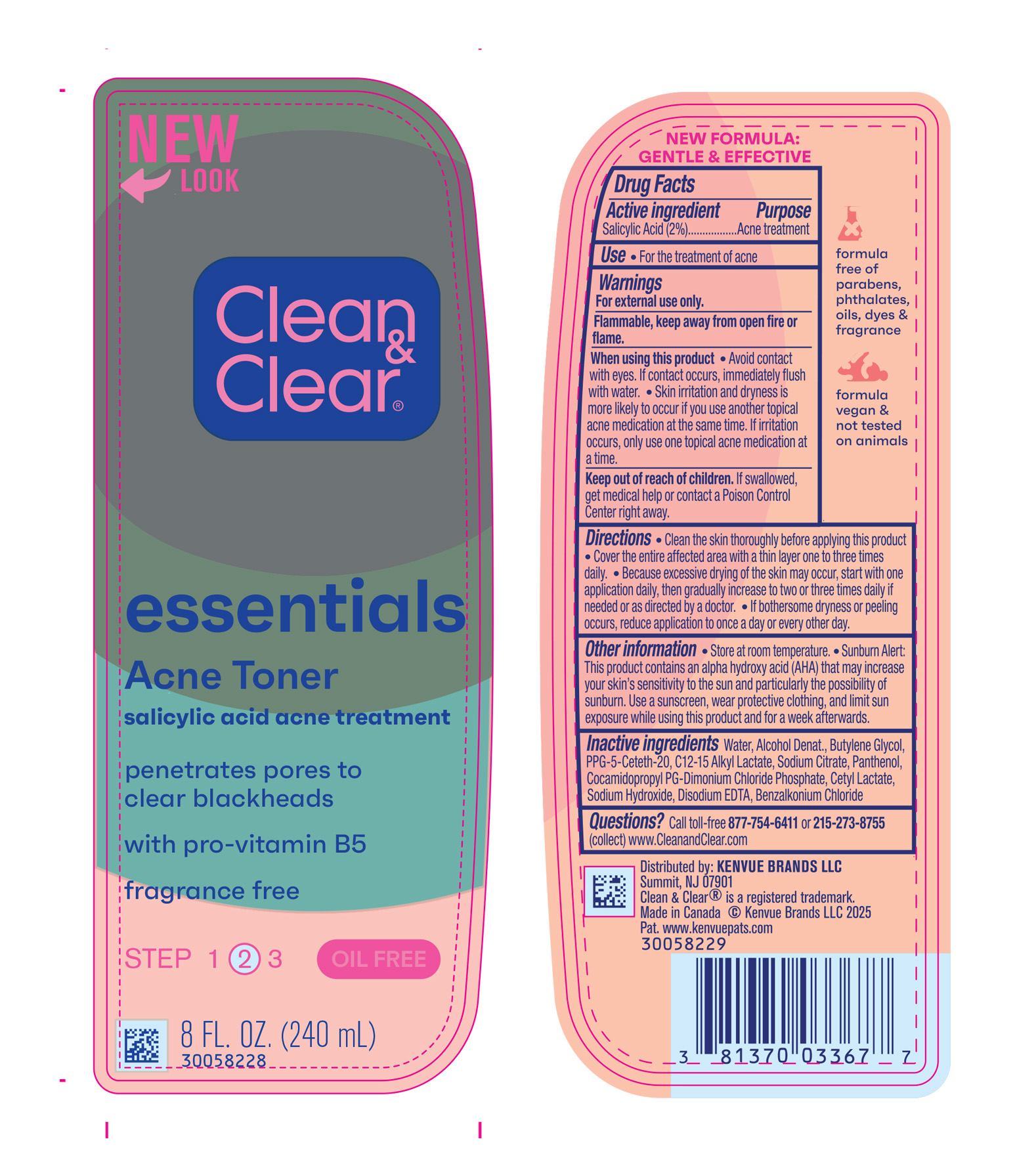 DRUG LABEL: Clean and Clear Essentials Acne Toner
NDC: 69968-0820 | Form: LIQUID
Manufacturer: Kenvue Brands LLC
Category: otc | Type: HUMAN OTC DRUG LABEL
Date: 20250418

ACTIVE INGREDIENTS: SALICYLIC ACID 20 mg/1 mL
INACTIVE INGREDIENTS: SODIUM CITRATE; WATER; PANTHENOL; C12-15 ALKYL LACTATE; COCAMIDOPROPYL PG-DIMONIUM CHLORIDE PHOSPHATE; CETYL LACTATE; EDETATE DISODIUM ANHYDROUS; BENZALKONIUM CHLORIDE; ALCOHOL; PPG-5-CETETH-20; BUTYLENE GLYCOL; SODIUM HYDROXIDE

Clean and Clear Essentials Acne Toner

Drug Facts

Active ingredient

Salicylic Acid (2%)

Purpose

Acne treatment

USE

- For the treatment of acne

WARNINGS

For external use only.

Flammable, keep away from open fire or flame.

When using this product

• Avoid contact with eyes. If contact occurs, immediately flush with water.

• Skin irritation and dryness is more likely to occur if you use another topical acne medication at the same time. If irritation occurs, only use one topical acne medication at a time.

Keep out of reach of children. If swallowed, get medical help or contact a Poison Control Center right away.

DIRECTIONS

• Clean the skin thoroughly before applying this product

• Cover the entire affected area with a thin layer one to three times daily.

• Because excessive drying of the skin may occur, start with one application daily, then gradually increase to two or three times daily if

needed or as directed by a doctor.

• If bothersome dryness or peeling occurs, reduce application to once a day or every other day.

OTHER INFORMATION

Store at Room Temperature.

Sunburn Alert: This product contains an alpha hydroxy acid (AHA) that may increase your skin’s sensitivity to the sun and particularly the possibility of sunburn. Use a sunscreen, wear protective clothing, and limit sun exposure while using this product and for a week afterwards.

INACTIVE INGREDIENTS

Water, Alcohol Denat., Butylene Glycol, PPG-5-Ceteth-20, C12-15 Alkyl Lactate, Sodium Citrate, Panthenol, Cocamidopropyl PG-Dimonium Chloride Phosphate, Cetyl Lactate, Sodium Hydroxide, Disodium EDTA, Benzalkonium Chloride

Questions?

Call toll-free 877-754-6411 or 215-273-8755 (collect) www.CleanandClear.com

Distributed by:
Kenvue Brands LLC
Summit, NJ 07901

PRINCIPAL DISPLAY PANEL - 240 mL Bottle Label

NEW

LOOK

Clean

&

Clear®

essentials

Acne Toner

salicylic acid acne treatment

penetrates pores to

clear blackheads

with pro-vitamin B5

fragrance free

STEP 1 ② 3

OIL FREE

8 FL. OZ. (240 mL)